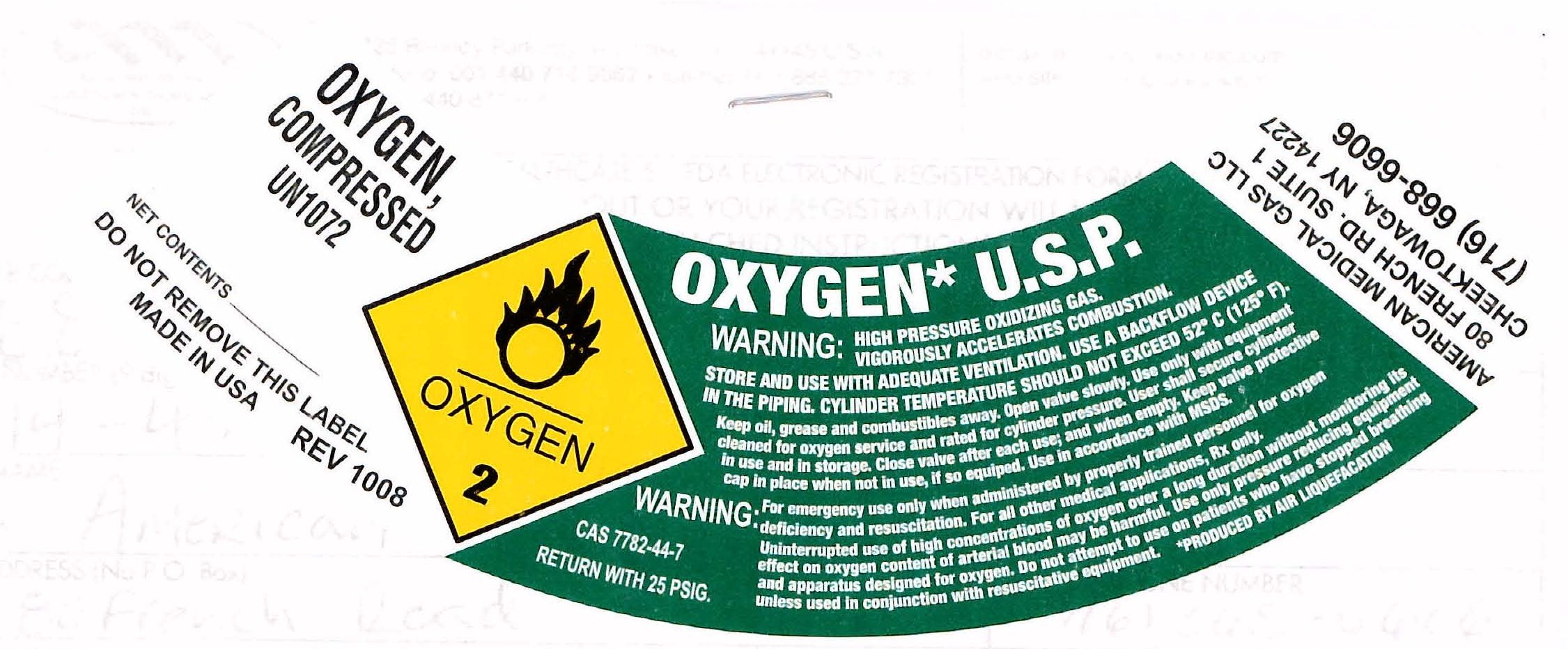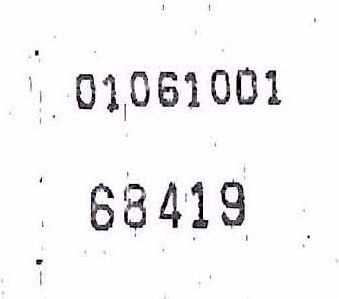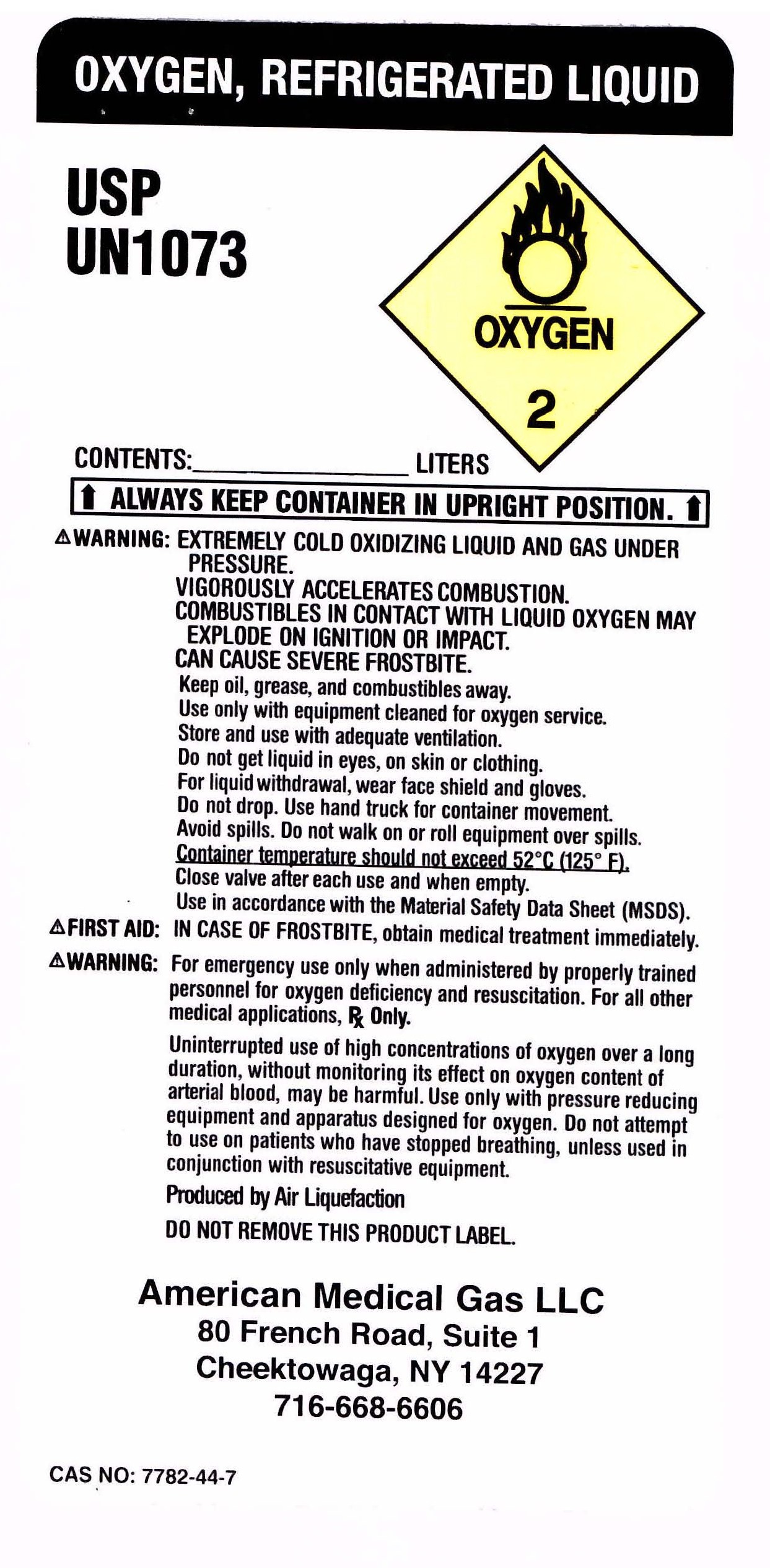 DRUG LABEL: Oxygen
NDC: 68419-0001 | Form: GAS
Manufacturer: American Medical Gas LLC
Category: prescription | Type: HUMAN PRESCRIPTION DRUG LABEL
Date: 20100112

ACTIVE INGREDIENTS: Oxygen 99 L/100 L

Oxygen